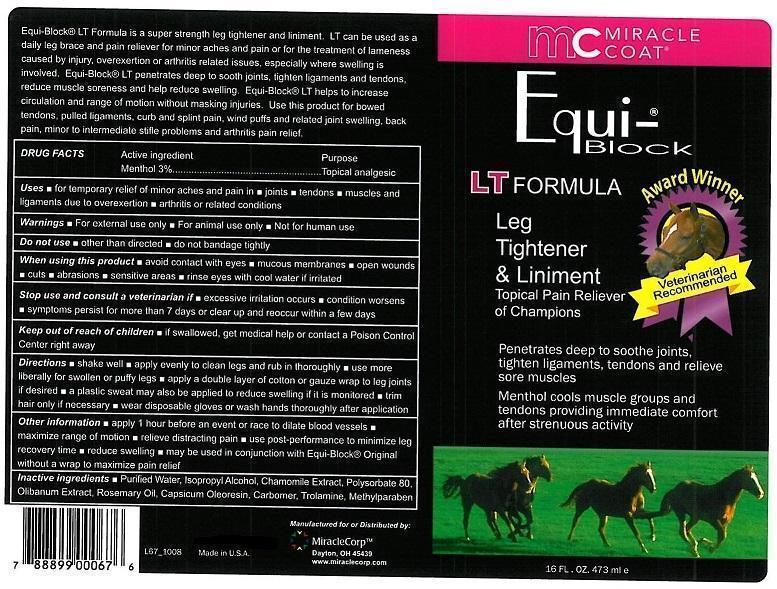 DRUG LABEL: EQUI-BLOCK
NDC: 61429-197 | Form: GEL
Manufacturer: MIRACLE CORP
Category: animal | Type: OTC ANIMAL DRUG LABEL
Date: 20200629

ACTIVE INGREDIENTS: MENTHOL 3 g/100 mL
INACTIVE INGREDIENTS: WATER; ISOPROPYL ALCOHOL; CHAMOMILE; POLYSORBATE 80; FRANKINCENSE; ROSEMARY OIL; CAPSICUM; CARBOMER 940; TROLAMINE; METHYLPARABEN

MIRACLE COAT - EQUI-BLOCK LT FORMULA - LEG TIGHTENER

ACTIVE INGREDIENT:

MENTHOL 3%

PURPOSE

TOPICAL ANALGESIC

USES

- FOR TEMPORARY RELIEF OF MINOR ACHES AND PAIN IN
- JOINTS
- TENDONS
- MUSCLES AND LIGAMENTS DUE TO OVEREXTENTION
- ARTHRITIS OR RELATED CONDITIONS

WARNINGS

- FOR EXTERNAL USE ONLY
- FOR ANIMAL USE ONLY
- NOT FOR HUMAN USE

DO NOT USE

- OTHER THAN DIRECTED
- DO NOT BANDAGE TIGHTLY

WHEN USING THIS PRODUCT

- AVOID CONTACT WITH EYES
- MUCOUS MEMBRANES
- OPEN WOUNDS
- CUTS
- ABRASIONS
- SENSITIVE AREAS
- RINSE EYES WITH COOL WATER IF IRRITATED

STOP USE AND CONSULT A VETERINARIAN IF

- EXCESSIVE IRRITATION OCCURS
- CONDITION WORSENS
- SYMPTOMS PERSIST FOR MORE THAN 7 DAYS OR CLEAR UP AND REOCCUR WITHIN A FEW DYS

KEEP OUT OF REACH OF CHILDREN.

- IF SWALLOWED, GET MEDICAL HELP OR CONTACT A POISON CONTROL CENTER RIGHT AWAY.

DIRECTIONS

- SHAKE WELL
- APPLY EVENLY TO CLEAN LEGS AND RUB IN THOROUGHLY
- USE MORE LIBERALLY FOR SWOLLEN OR PUFFY LEGS
- APPLY A DOUBLE LAYER OF COTTON OR GAUZE WRAP TO LEG JOINTS IF DESIRED
- A PLASTIC SWEAT MAY ALSO BE APPLIED TO REDUCE SWELLING IF IT IS MONITORED
- TRIM HAIR ONLY IF NECESSRY
- WEAR DISPOSABLE GLOVES OR WASH HANDS THOROUGHLY AFTER APPLICATION

OTHER INFORMATION

- APPLY 1 HOUR BEFORE AN EVENT OR RACE TO DILATE BLOOD VESSELS
- MAXIMIZE RANGE OF MOTION
- RELIEVE DISTRACTING PAIN
- USE POST-PERFORMANCE TO MINIMIZE LEG RECOVERY TIME
- REDUCE SWELLING
- MAY BE USED N CONJUNCTION WITH EQUI-BLOCK ORIGINAL WITHOUT A WRAP TO MAXIMIZE PAIN RELIEF

INACTIVE INGREDENTS

- PURIFIED WATER, ISOPROPYL ALCOHOL, CHAMOMILE EXTRACT, POLYSORBATE 80, OLIBANUM EXTRACT, ROSEMARY OIL, CAPSICUM OLEORESIN, CARBOMER, TROLAMINE, METHYLPARABEN